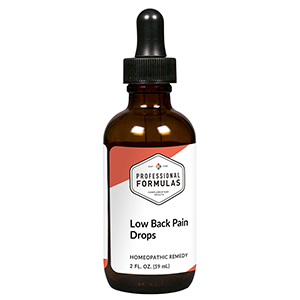 DRUG LABEL: Low Back Pain Drops
NDC: 63083-2041 | Form: LIQUID
Manufacturer: Professional Complementary Health Formulas
Category: homeopathic | Type: HUMAN OTC DRUG LABEL
Date: 20190815

ACTIVE INGREDIENTS: APIS MELLIFERA 6 [hp_X]/59 mL; BERBERIS VULGARIS ROOT BARK 6 [hp_X]/59 mL; BOS TAURUS HYPOTHALAMUS 6 [hp_X]/59 mL; POTASSIUM DICHROMATE 6 [hp_X]/59 mL; BOS TAURUS BONE MARROW 6 [hp_X]/59 mL; LYCOPODIUM CLAVATUM SPORE 6 [hp_X]/59 mL; MAGNESIUM PHOSPHATE, DIBASIC TRIHYDRATE 6 [hp_X]/59 mL; BOS TAURUS SOMATIC NERVE 6 [hp_X]/59 mL; SEPIA OFFICINALIS JUICE 6 [hp_X]/59 mL; ACONITUM NAPELLUS WHOLE 6 [hp_X]/59 mL; AMARYLLIS BELLADONNA WHOLE 6 [hp_X]/59 mL; CAUSTICUM 6 [hp_X]/59 mL; TOXICODENDRON PUBESCENS LEAF 6 [hp_X]/59 mL; ARNICA MONTANA WHOLE 6 [hp_X]/59 mL; ATROPINE 12 [hp_X]/59 mL; GRAPHITE 12 [hp_X]/59 mL; HYPERICUM PERFORATUM WHOLE 30 [hp_X]/59 mL
INACTIVE INGREDIENTS: ALCOHOL; WATER

C41

ACTIVE INGREDIENTS

Apis mellifica 6X
Berberis vulgaris 6X
Hypothalamus 6X
Kali bichromicum 6X
Lumbar vertebrae 6X
Lycopodium clavatum 6X
Magnesia phosphorica 6X
Sciatic nerve 6X
Sepia 6X
Aconitum napellus 6X, 12X
Belladonna 6X, 12X
Causticum 6X, 12X
Rhus toxicodendron 6X, 12X, 30X
Arnica montana 6X, 30X, 60X
Atropinum 12X
Graphites 12X
Hypericum perforatum 30X

QUESTIONS

Professional Formulas

PO Box 2034 Lake Oswego, OR 97035

INDICATIONS

For the temporary relief of minor pain or stiffness in the lower back.*

PURPOSE

*Claims based on traditional homeopathic practice, not accepted medical evidence. Not FDA evaluated.

WARNINGS

In case of overdose, get medical help or contact a poison control center right away.

Keep out of the reach of children.

PREGNANCY OR BREAST FEEDING

If pregnant or breastfeeding, ask a healthcare professional before use.

DIRECTIONS

Place drops under tongue 30 minutes before/after meals. Adults and children 12 years and over: Take 10 drops up to 3 times per day for up to 6 weeks. For immediate onset of symptoms, take 10 to 15 drops every 15 minutes up to 3 hours. For less severe symptoms, take 10-15 drops hourly up to 8 hours. Consult a physician for use in children under 12 years of age.

OTHER INFORMATION

Tamper resistant. If seal is broken, do not use. After opening, close container tightly and store at room temperature away from heat.

INACTIVE INGREDIENTS

20% ethanol, purified water.

LABEL

Est 1985

Professional Formulas

Complementary Health

Low Back Pain Drops

Homeopathic Remedy

2 FL. OZ. (59 mL)